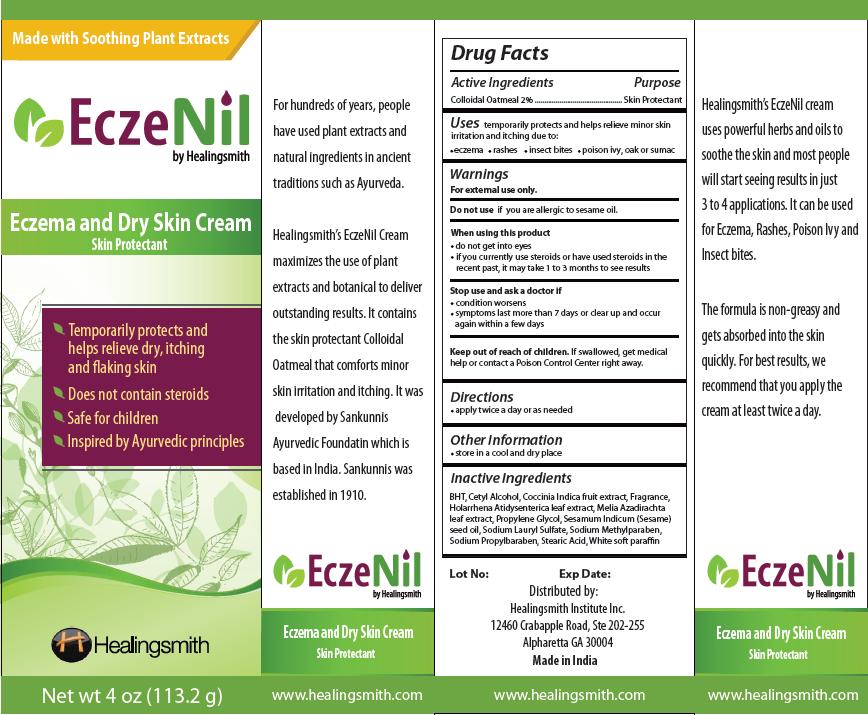 DRUG LABEL: EczeNil
NDC: 76066-001 | Form: CREAM
Manufacturer: Healingsmith Institute Inc.
Category: otc | Type: HUMAN OTC DRUG LABEL
Date: 20111011

ACTIVE INGREDIENTS: OATMEAL 2.3 g/113.2 g
INACTIVE INGREDIENTS: BUTYLATED HYDROXYTOLUENE; CETYL ALCOHOL; COCCINIA GRANDIS FRUIT; PROPYLENE GLYCOL; AZADIRACHTA INDICA LEAF; SESAME OIL; SODIUM LAURYL SULFATE; METHYLPARABEN SODIUM; PROPYLPARABEN SODIUM; STEARIC ACID; PARAFFIN

ACTIVE INGREDIENT

Colloidal Oatmeal 2%

PURPOSE

Skin Protectant

Uses
temporarily protects and helps relieve minor skin irritation and itching due to:

- eczema
- rashes
- insect bites
- poison ivy, oak or sumac

Warnings
For external use only.

Do not use if you are allergic to sesame oil.

When using this product

- do not get into eyes
- if you currently use steroids or have used steroids in the recent past, it may take 1 to 3 months to see results

Stop use and ask a doctor if

- condition worsens
- symptoms last more than 7 days or clear up and occur again within a few days

Keep out of reach of children. If swallowed, get medical help or contact a Poison Control Center right away.

Directions

- apply twice a day or as needed

Other Information

- store in a cool and dry place

Inactive Ingredients
BHT, Cetyl Alcohol, Coccinia Indica fruit extract, Fragrance, Holarrhena Atidysenterica leaf extract, Melia Azadirachta leaf extract, Propylene Glycol, Sesamum Indicum (Sesame) seed oil, Sodium Lauryl Sulfate, Sodium Methylparaben, Sodium Propylbaraben, Stearic Acid, White soft paraffin